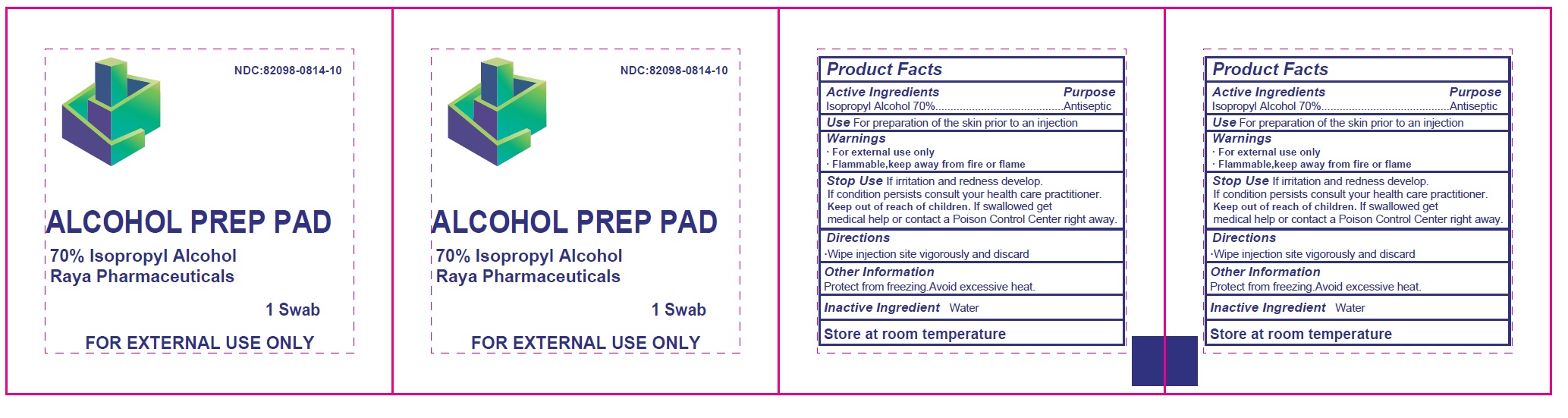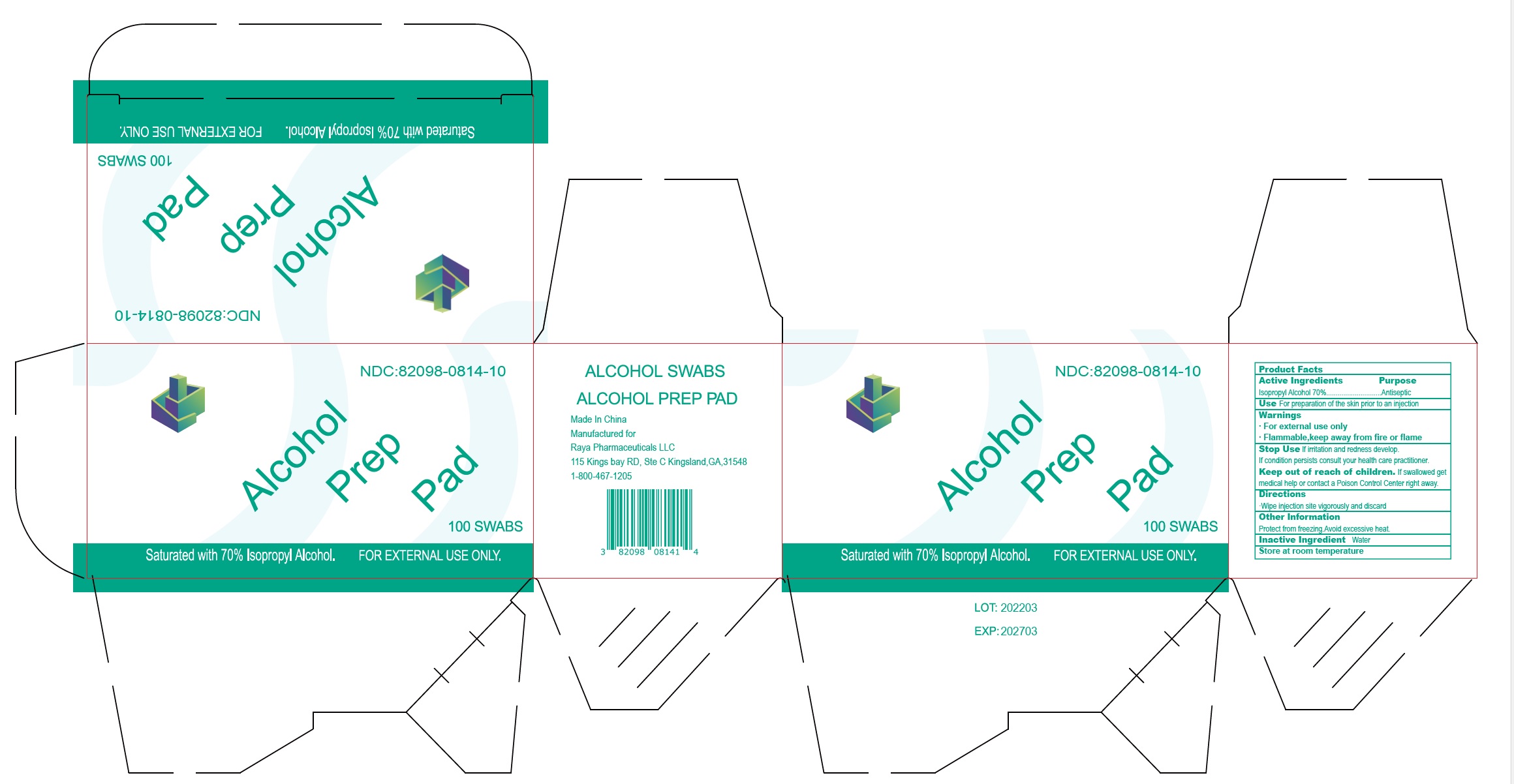 DRUG LABEL: Alcohol Prep Pads
NDC: 82098-814 | Form: SWAB
Manufacturer: Raya Pharmaceuticals LLC
Category: otc | Type: HUMAN OTC DRUG LABEL
Date: 20231027

ACTIVE INGREDIENTS: ISOPROPYL ALCOHOL 0.7 mL/1 mL
INACTIVE INGREDIENTS: WATER

Alcohol Prep Pads
70%Isopropyl Alcohol Pads

INDICATIONS AND USAGE

For the preparation of the skin prior to an injection

Wipe injection site vigorously and discard

PRECAUTIONS

- For external use only
- Flammable, keep away from fire or flame

Warnings
· For external use only
· Flammable, keep away from fire or flame

Stop Use

· If irritation and redness develop.
· If the condition persists consult your health care practitioner.

· Keep out of reach of children. If swallowed get medical help or contact a Poison Control Center right away.

STORAGE AND HANDLING

Store at room temperature

Protect from freezing. Avoid excessive heat.

Dosage and Administration

Wipe injection site vigorously and discard

WARNINGS

For External Use

Flamable, Keep Away from fire and flame

Inactive ingredients

Water

Keep out of reach of children, if swallowed get medical help or contact a poison center right away.

Purpose section

Use for preperation of the skin prioir to an injection

Isopropyl Alcohol 70%........................Purpose: Antiseptic

Active ingredients

Isopropyl Alcohol 70%........................Antiseptic

PACKAGE LABEL

ALCOHOL PREP PAD

Saturated with 70% Isopropyl Alcohol

100 Swabs

For External use only